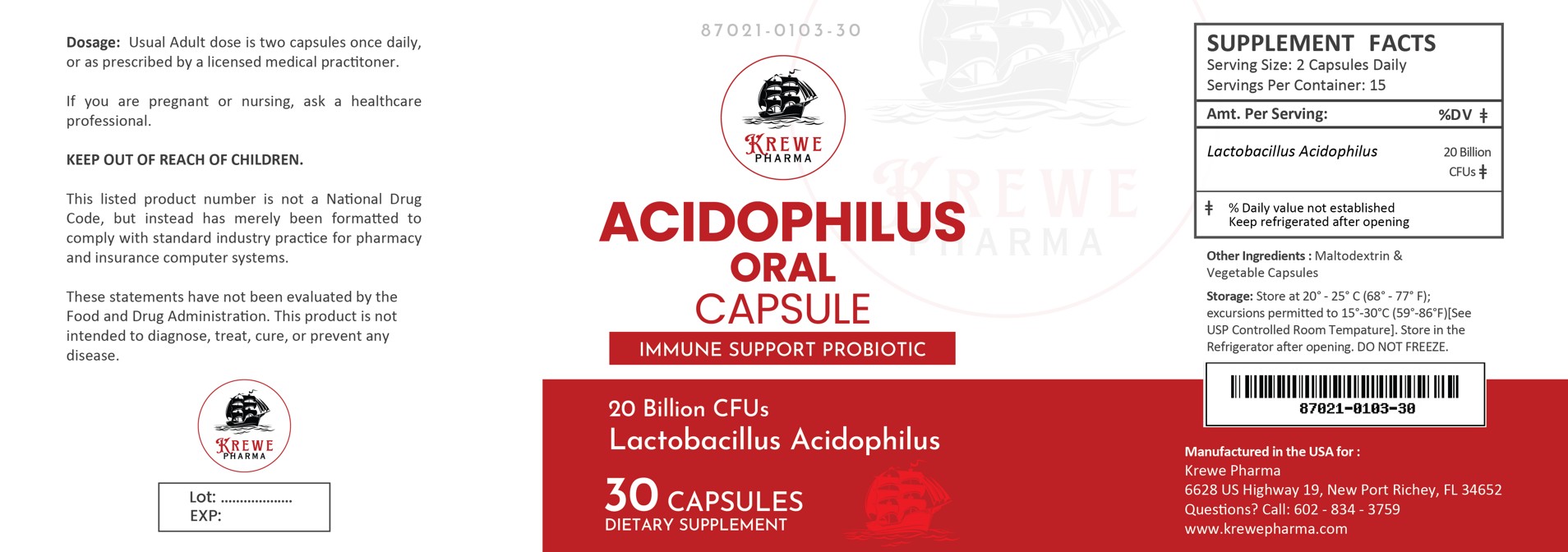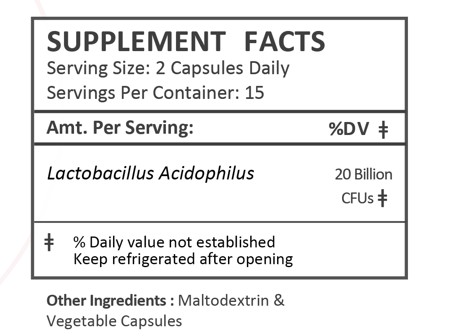 DRUG LABEL: ACIDOPHILUS
NDC: 87021-103 | Form: CAPSULE
Manufacturer: Krewe Pharma, LLC
Category: other | Type: DIETARY SUPPLEMENT
Date: 20251113

ACTIVE INGREDIENTS: LACTOBACILLUS ACIDOPHILUS 10000000000 [CFU]/1 1

Acidophilus Oral Capsule

HEALTH CLAIM:

Acidophilus Oral Capsule

DESCRIPTION:

Acidophilus Oral Capsules are clear capsules dispensed in plastic bottles of 30 ct.

87021-0103-30

Reserved for Professional Recommendation

This listed product is not a National Drug Code, but instead has merely been formatted to comply with standard industry practice for pharmacy and insurance computer systems.

These statements have not been evaluated by the Food and Drug Administration. This product is not intended to diagnose, treat, cure or prevent any disease.

All prescriptions using this product shall be pursuant to state statutes as applicable. This is not an Orange Book product. This product may be administered only under a physician’s supervision. There are no implied or explicit claims on therapeutic equivalence.

Manufactured for:

Krewe Pharma

New Port Richey, FL 34652

WARNINGS AND PRECAUTIONS:

This product is contraindicated in patients with a known hypersensitivity to any of the ingredients.

As with any supplement, if you are pregnant, nursing, taking medication, or have a medical condition, ask a health professional before taking this product.

These statements have not been evaluated by the Food and Drug Administration. This product is not intended to diagnose, treat, cure, or prevent any disease.

DOSAGE AND ADMINISTRATION:

Usual adult dose is 2 capsules by mouth daily once daily, or as prescribed by a licensed medical practitioner.

PRECAUTIONS:

CONTRAINDICATIONS
This product is contraindicated in patients with known hypersensitivity to any of the ingredients.

PRECAUTIONS
This product is contraindicated in patients with a known hypersensitivity to any of the ingredients.

ADVERSE REACTIONS
Allergic sensitizations have been reported following oral administration of folic acid. Consult your physician immediately if adverse side effects occur.

KEEP OUT OF THE REACH OF CHILDREN.

STORAGE:

Store at 20° - 25° C (68° - 77° F); excursions permitted to 15°-30°C (59°-86°F)[See USP Controlled Room Tempature].

Store in the Refrigerator after opening. DO NOT FREEZE.